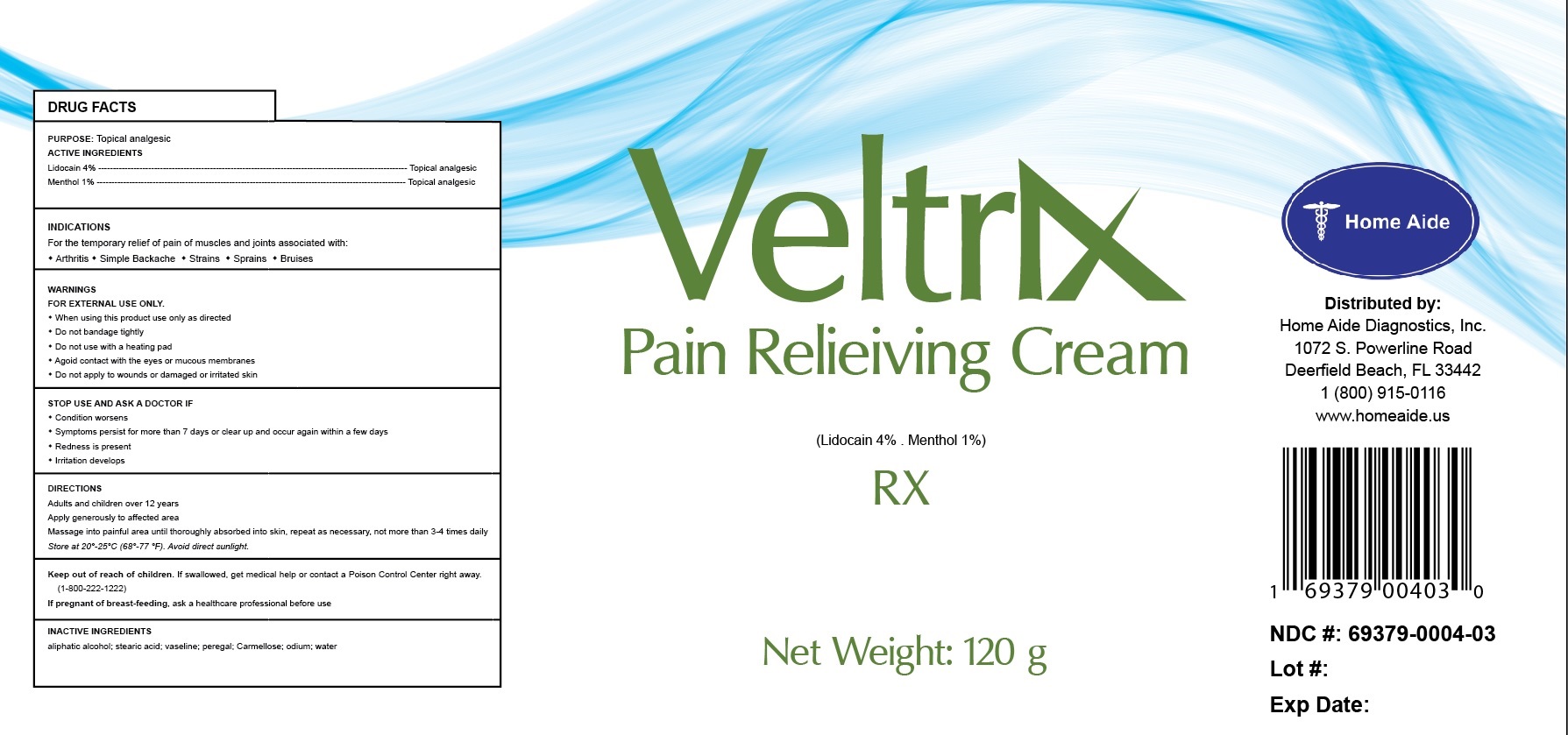 DRUG LABEL: Veltrix
NDC: 69379-004 | Form: CREAM
Manufacturer: Home Aide Diagnostics, Inc.
Category: prescription | Type: HUMAN PRESCRIPTION DRUG LABEL
Date: 20150713

ACTIVE INGREDIENTS: LIDOCAINE 4 g/100 g; MENTHOL 1 g/100 g

Veltrix Pain Relieiving Cream

PATIENT COUNSELING INFORMATION

PURPOSE: Topical analgesic

ACTIVE INGREDIENTS
Lidocain 4% --------------------------------------------------------------------------------------------------------- Topical analgesic
Menthol 1% --------------------------------------------------------------------------------------------------------- Topical analgesic

INDICATIONS
For the temporary relief of pain of muscles and joints associated with:

- Arthritis
- Simple Backache
- Strains
- Sprains
- Bruises

DIRECTIONS
Adults and children over 12 years
Apply generously to affected area
Massage into painful area until thoroughly absorbed into skin, repeat as necessary, not more than 3-4 times daily
Store at 20°-25°C (68°-77 °F). Avoid direct sunlight.

WARNINGS
FOR EXTERNAL USE ONLY.

- When using this product use only as directed
- Do not bandage tightly
- Do not use with a heating pad
- Agoid contact with the eyes or mucous membranes
- Do not apply to wounds or damaged or irritated skin

STOP USE AND ASK A DOCTOR IF

- Condition worsens
- Symptoms persist for more than 7 days or clear up and occur again within a few days
- Redness is present
- Irritation develops

- Keep out of reach of children. If swallowed, get medical help or contact a Poison Control Center right away. (1-800-222-1222)
- If pregnant of breast-feeding, ask a healthcare professional before use

INACTIVE INGREDIENTS
aliphatic alcohol; stearic acid; vaseline; peregal; Carmellose; odium; water